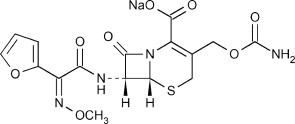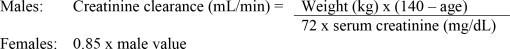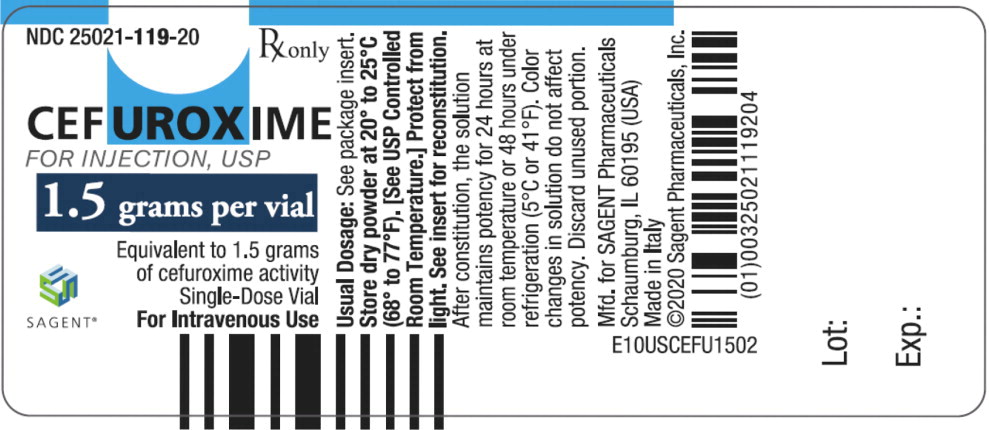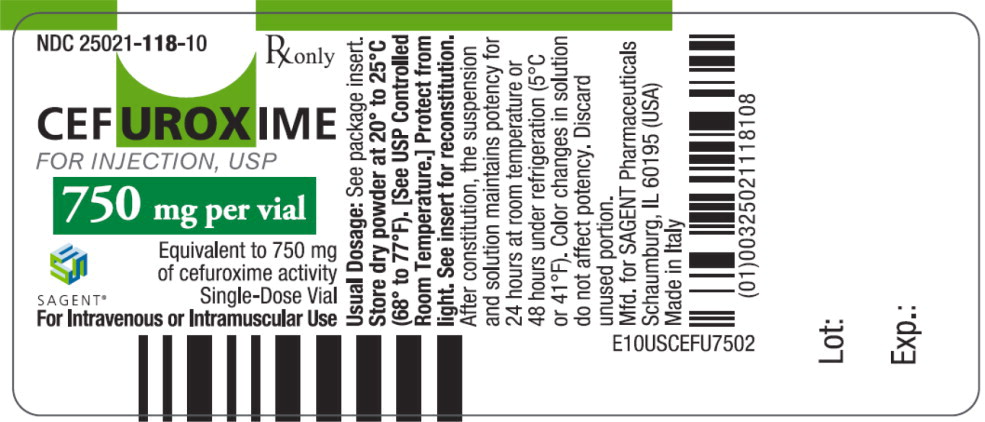 DRUG LABEL: Cefuroxime sodium
NDC: 25021-118 | Form: INJECTION, POWDER, FOR SOLUTION
Manufacturer: Sagent Pharmaceuticals
Category: prescription | Type: HUMAN PRESCRIPTION DRUG LABEL
Date: 20250204

ACTIVE INGREDIENTS: cefuroxime sodium 750 mg/1 1

Cefuroxime for Injection, USP

SAGENT®
Rx only

To reduce the development of drug-resistant bacteria and maintain the effectiveness of Cefuroxime for Injection and other antibacterial drugs, Cefuroxime for Injection should be used only to treat or prevent infections that are proven or strongly suspected to be caused by bacteria.

DESCRIPTION

Cefuroxime is a sterile semisynthetic, broad-spectrum, cephalosporin antibiotic for parenteral administration. It is the sodium salt of (6R,7R)-3-[(carbamoyloxy)methyl]-7-[[(Z)-(furan-2-yl) (methoxyimino)acetyl] amino]-8-oxo-5-thia-1-azabicyclo[4.2.0]oct-2-ene-2-carboxylate, and it has the following chemical structure:

The empirical formula is C16H15N4NaO8S, representing a molecular weight of 446.37.

Cefuroxime for Injection, USP contains approximately 54.2 mg (2.4 mEq) of sodium per gram of cefuroxime activity.

Cefuroxime for Injection, USP in sterile crystalline form is supplied in vials equivalent to 750 mg or 1.5 g of cefuroxime as cefuroxime sodium. Solutions of Cefuroxime for Injection, USP range in color from light yellow to amber, depending on the concentration and diluent used. The pH of freshly constituted solutions usually ranges from 6 to 8.5.

CLINICAL PHARMACOLOGY

After intramuscular (IM) injection of a 750-mg dose of cefuroxime to normal volunteers, the mean peak serum concentration was 27 mcg/mL. The peak occurred at approximately 45 minutes (range, 15 to 60 minutes). Following IV doses of 750 mg and 1.5 g, serum concentrations were approximately 50 and 100 mcg/mL, respectively, at 15 minutes. Therapeutic serum concentrations of approximately 2 mcg/mL or more were maintained for 5.3 hours and 8 hours or more, respectively. There was no evidence of accumulation of cefuroxime in the serum following IV administration of 1.5-g doses every 8 hours to normal volunteers. The serum half-life after either IM or IV injections is approximately 80 minutes.

Approximately 89% of a dose of cefuroxime is excreted by the kidneys over an 8-hour period, resulting in high urinary concentrations.

Following the IM administration of a 750-mg single dose, urinary concentrations averaged 1,300 mcg/mL during the first 8 hours. Intravenous doses of 750 mg and 1.5 g produced urinary levels averaging 1,150 and 2,500 mcg/mL, respectively, during the first 8-hour period.

The concomitant oral administration of probenecid with cefuroxime slows tubular secretion, decreases renal clearance by approximately 40%, increases the peak serum level by approximately 30%, and increases the serum half-life by approximately 30%. Cefuroxime is detectable in therapeutic concentrations in pleural fluid, joint fluid, bile, sputum, bone, and aqueous humor.

Cefuroxime is detectable in therapeutic concentrations in cerebrospinal fluid (CSF) of adults and pediatric patients with meningitis. The following table shows the concentrations of cefuroxime achieved in cerebrospinal fluid during multiple dosing of patients with meningitis.

Table 1. Concentrations of Cefuroxime Achieved in Cerebrospinal Fluid During Multiple Dosing of Patients with Meningitis
Patients | Dose | Number of Patients | Mean (Range) CSF Cefuroxime Concentrations (mcg/mL) Achieved Within 8 Hours Post Dose
Pediatric patients (4 weeks to 6.5 years) | 200 mg/kg/day, divided q 6 hours | 5 | 6.6 (0.9 to 17.3)
Pediatric patients (7 months to 9 years) | 200 to 230 mg/kg/day, divided q 8 hours | 6 | 8.3 (< 2 to 22.5)
Adults | 1.5 grams q 8 hours | 2 | 5.2 (2.7 to 8.9)
Adults | 1.5 grams q 6 hours | 10 | 6 (1.5 to 13.5)

Cefuroxime is approximately 50% bound to serum protein.

Microbiology

Mechanism of Action

Cefuroxime is a bactericidal agent that acts by inhibition of bacterial cell wall synthesis. Cefuroxime has activity in the presence of some beta-lactamases, both penicillinases and cephalosporinases, of Gram-negative and Gram-positive bacteria.

Mechanism of Resistance

Resistance to cefuroxime is primarily through hydrolysis by beta-lactamase, alteration of penicillin-binding proteins (PBPs), and decreased permeability.

Interaction with Other Antimicrobials

In an in vitro study antagonistic effects have been observed with the combination of chloramphenicol and cefuroxime.

Cefuroxime has been shown to be active against most isolates of the following bacteria, both in vitro and in clinical infections as described in the INDICATIONS AND USAGE section:

Gram-negative bacteria

- Enterobacter spp.
- Escherichia coli
- Klebsiella spp.
- Haemophilus influenzae
- Neisseria meningitidis
- Neisseria gonorrhoeae

Gram-positive bacteria

- Staphylococcus aureus
- Streptococcus pneumoniae
- Streptococcus pyogenes

The following in vitro data are available, but their clinical significance is unknown. At least 90 percent of the following bacteria exhibit an in vitro minimum inhibitory concentration (MIC) less than or equal to the susceptible breakpoint for cefuroxime against isolates of similar genus or organism group. However, the efficacy of cefuroxime in treating clinical infections caused by these bacteria has not been established in adequate and well-controlled clinical trials.

Gram-negative bacteria

- Citrobacter spp.
- Providencia rettgeri
- Haemophilus parainfluenzae
- Proteus mirabilis
- Moraxella catarrhalis
- Morganella morganii
- Salmonella spp.
- Shigella spp.

Gram-positive bacteria

- Staphylococcus epidermidis

Susceptibility Testing

For specific information regarding susceptibility test interpretive criteria and associated test methods and quality control standards recognized by FDA for this drug, please see: https://www.fda.gov/STIC.

INDICATIONS AND USAGE

Cefuroxime for Injection, USP is indicated for the treatment of patients with infections caused by susceptible strains of the designated organisms in the following diseases:

1. Lower Respiratory Tract Infections, including pneumonia, caused by Streptococcus pneumoniae, Haemophilus influenzae (including ampicillin-resistant strains), Klebsiella spp., Staphylococcus aureus (penicillinase- and non-penicillinase- producing strains), Streptococcus pyogenes, and Escherichia coli.
2. Urinary Tract Infections caused by Escherichia coli and Klebsiella spp.
3. Skin and Skin-Structure Infections caused by Staphylococcus aureus (penicillinase- and non-penicillinase-producing strains), Streptococcus pyogenes, Escherichia coli, Klebsiella spp., and Enterobacter spp.
4. Septicemia caused by Staphylococcus aureus (penicillinase- and non-penicillinase- producing strains), Streptococcus pneumoniae, Escherichia coli, Haemophilus influenzae (including ampicillin-resistant strains), and Klebsiella spp.
5. Meningitis caused by Streptococcus pneumoniae, Haemophilus influenzae (including ampicillin-resistant strains), Neisseria meningitidis, and Staphylococcus aureus (penicillinase- and non-penicillinase-producing strains).
6. Gonorrhea: Uncomplicated and disseminated gonococcal infections due to Neisseria gonorrhoeae (penicillinase- and non-penicillinase-producing strains) in both males and females.
7. Bone and Joint Infections caused by Staphylococcus aureus (penicillinase- and non- penicillinase-producing strains).

Clinical microbiological studies in skin and skin-structure infections frequently reveal the growth of susceptible strains of both aerobic and anaerobic organisms. Cefuroxime for Injection, USP has been used successfully in these mixed infections in which several organisms have been isolated.

In certain cases of confirmed or suspected gram-positive or gram-negative sepsis or in patients with other serious infections in which the causative organism has not been identified, Cefuroxime for Injection, USP may be used concomitantly with an aminoglycoside (see PRECAUTIONS). The recommended doses of both antibiotics may be given depending on the severity of the infection and the patient's condition.

To reduce the development of drug-resistant bacteria and maintain the effectiveness of Cefuroxime for Injection, USP and other antibacterial drugs, Cefuroxime for Injection, USP should be used only to treat or prevent infections that are proven or strongly suspected to be caused by susceptible bacteria. When culture and susceptibility information are available, they should be considered in selecting or modifying antibacterial therapy. In the absence of such data, local epidemiology and susceptibility patterns may contribute to the empiric selection of therapy.

Prevention

The preoperative prophylactic administration of Cefuroxime for Injection, USP may prevent the growth of susceptible disease-causing bacteria and thereby may reduce the incidence of certain postoperative infections in patients undergoing surgical procedures (e.g., vaginal hysterectomy) that are classified as clean-contaminated or potentially contaminated procedures. Effective prophylactic use of antibiotics in surgery depends on the time of administration. Cefuroxime for Injection, USP should usually be given one-half to 1 hour before the operation to allow sufficient time to achieve effective antibiotic concentrations in the wound tissues during the procedure. The dose should be repeated intraoperatively if the surgical procedure is lengthy.

Prophylactic administration is usually not required after the surgical procedure ends and should be stopped within 24 hours. In the majority of surgical procedures, continuing prophylactic administration of any antibiotic does not reduce the incidence of subsequent infections but will increase the possibility of adverse reactions and the development of bacterial resistance.

The perioperative use of Cefuroxime for Injection, USP has also been effective during open heart surgery for surgical patients in whom infections at the operative site would present a serious risk. For these patients it is recommended that therapy with Cefuroxime for Injection, USP be continued for at least 48 hours after the surgical procedure ends. If an infection is present, specimens for culture should be obtained for the identification of the causative organism, and appropriate antimicrobial therapy should be instituted.

CONTRAINDICATIONS

Cefuroxime for Injection is contraindicated in patients with known allergy to the cephalosporin group of antibiotics.

WARNINGS

BEFORE THERAPY WITH CEFUROXIME FOR INJECTION IS INSTITUTED, CAREFUL INQUIRY SHOULD BE MADE TO DETERMINE WHETHER THE PATIENT HAS HAD PREVIOUS HYPERSENSITIVITY REACTIONS TO CEPHALOSPORINS, PENICILLINS, OR OTHER DRUGS. THIS PRODUCT SHOULD BE GIVEN CAUTIOUSLY TO PENICILLIN-SENSITIVE PATIENTS. ANTIBIOTICS SHOULD BE ADMINISTERED WITH CAUTION TO ANY PATIENT WHO HAS DEMONSTRATED SOME FORM OF ALLERGY, PARTICULARLY TO DRUGS. IF AN ALLERGIC REACTION TO CEFUROXIME FOR INJECTION OCCURS, DISCONTINUE THE DRUG. SERIOUS ACUTE HYPERSENSITIVITY REACTIONS MAY REQUIRE EPINEPHRINE AND OTHER EMERGENCY MEASURES.

Clostridioides difficile associated diarrhea (CDAD) has been reported with use of nearly all antibacterial agents, including Cefuroxime for Injection, and may range in severity from mild diarrhea to fatal colitis. Treatment with antibacterial agents alters the normal flora of the colon leading to overgrowth of C. difficile.

C. difficile produces toxins A and B which contribute to the development of CDAD. Hypertoxin producing strains of C. difficile cause increased morbidity and mortality, as these infections can be refractory to antimicrobial therapy and may require colectomy. CDAD must be considered in all patients who present with diarrhea following antibiotic use. Careful medical history is necessary since CDAD has been reported to occur over two months after the administration of antibacterial agents.

If CDAD is suspected or confirmed, ongoing antibiotic use not directed against C. difficile may need to be discontinued. Appropriate fluid and electrolyte management, protein supplementation, antibiotic treatment of C. difficile, and surgical evaluation should be instituted as clinically indicated.

When the colitis is not relieved by drug discontinuation or when it is severe, oral vancomycin is the treatment of choice for antibiotic-associated pseudomembranous colitis produced by Clostridioides difficile. Other causes of colitis should also be considered.

PRECAUTIONS

General

Although Cefuroxime for Injection rarely produces alterations in kidney function, evaluation of renal status during therapy is recommended, especially in seriously ill patients receiving the maximum doses. Cephalosporins should be given with caution to patients receiving concurrent treatment with potent diuretics as these regimens are suspected of adversely affecting renal function.

The total daily dose of Cefuroxime for Injection should be reduced in patients with transient or persistent renal insufficiency (see DOSAGE AND ADMINISTRATION), because high and prolonged serum antibiotic concentrations can occur in such individuals from usual doses.

As with other antibiotics, prolonged use of Cefuroxime for Injection may result in overgrowth of nonsusceptible organisms. Careful observation of the patient is essential. If superinfection occurs during therapy, appropriate measures should be taken.

Broad-spectrum antibiotics should be prescribed with caution in individuals with a history of gastrointestinal disease, particularly colitis.

Nephrotoxicity has been reported following concomitant administration of aminoglycoside antibiotics and cephalosporins.

As with other therapeutic regimens used in the treatment of meningitis, mild-to-moderate hearing loss has been reported in a few pediatric patients treated with cefuroxime. Persistence of positive CSF (cerebrospinal fluid) cultures at 18 to 36 hours has also been noted with cefuroxime injection, as well as with other antibiotic therapies; however, the clinical relevance of this is unknown.

Cephalosporins may be associated with a fall in prothrombin activity. Those at risk include patients with renal or hepatic impairment, or poor nutritional state, as well as patients receiving a protracted course of antimicrobial therapy, and patients previously stabilized on anticoagulant therapy. Prothrombin time should be monitored in patients at risk and exogenous Vitamin K administered as indicated.

Prescribing Cefuroxime for Injection in the absence of a proven or strongly suspected bacterial infection or a prophylactic indication is unlikely to provide benefit to the patient and increases the risk of the development of drug-resistant bacteria.

Information for Patients

Patients should be counseled that antibacterial drugs, including Cefuroxime for Injection should only be used to treat bacterial infections. They do not treat viral infections (e.g., the common cold). When Cefuroxime for Injection is prescribed to treat a bacterial infection, patients should be told that although it is common to feel better early in the course of therapy, the medication should be taken exactly as directed. Skipping doses or not completing the full course of therapy may: (1) decrease the effectiveness of the immediate treatment, and (2) increase the likelihood that bacteria will develop resistance and will not be treatable by Cefuroxime for Injection or other antibacterial drugs in the future.

Diarrhea is a common problem caused by antibiotics which usually ends when the antibiotic is discontinued. Sometimes after starting treatment with antibiotics, patients can develop watery and bloody stools (with or without stomach cramps and fever) even as late as 2 or more months after having taken the last dose of the antibiotic. If this occurs, patients should contact their physician as soon as possible.

Drug/Laboratory Test Interactions

A false-positive reaction for glucose in the urine may occur with copper reduction tests (Benedict's or Fehling's solution or with CLINITEST® tablets) but not with enzyme-based tests for glycosuria. As a false-negative result may occur in the ferricyanide test, it is recommended that either the glucose oxidase or hexokinase method be used to determine blood plasma glucose levels in patients receiving Cefuroxime for Injection.

Cefuroxime does not interfere with the assay of serum and urine creatinine by the alkaline picrate method.

Carcinogenesis, Mutagenesis, Impairment of Fertility

Although lifetime studies in animals have not been performed to evaluate carcinogenic potential, no mutagenic activity was found for cefuroxime in the mouse lymphoma assay and a battery of bacterial mutation tests. Positive results were obtained in an in vitro chromosome aberration assay; however, negative results were found in an in vivo micronucleus test at doses up to 10 g/kg. Reproduction studies in mice at doses up to 3,200 mg/kg/day (3.1 times the recommended maximum human dose based on mg/m^2) have revealed no impairment of fertility.

Reproductive studies revealed no impairment of fertility in animals.

Pregnancy

Teratogenic Effects

Pregnancy Category B. Reproduction studies have been performed in mice at doses up to 6,400 mg/kg/day (6.3 times the recommended maximum human dose based on mg/m^2) and rabbits at doses up to 400 mg/kg/day (2.1 times the recommended maximum human dose based on mg/m^2) and have revealed no evidence of impaired fertility or harm to the fetus due to cefuroxime. There are, however, no adequate and well-controlled studies in pregnant women. Because animal reproduction studies are not always predictive of human response, this drug should be used during pregnancy only if clearly needed.

Nursing Mothers

Since cefuroxime is excreted in human milk, caution should be exercised when Cefuroxime for Injection is administered to a nursing woman.

Pediatric Use

Safety and effectiveness in pediatric patients below 3 months of age have not been established. Accumulation of other members of the cephalosporin class in newborn infants (with resulting prolongation of drug half-life) has been reported.

Geriatric Use

Of the 1,914 subjects who received cefuroxime in 24 clinical studies of Cefuroxime for Injection, 901 (47%) were 65 years and older while 421 (22%) were 75 years and older. No overall differences in safety or effectiveness were observed between these subjects and younger subjects, and other reported clinical experience has not identified differences in responses between the elderly and younger patients, but greater susceptibility of some older individuals to drug effects cannot be ruled out. This drug is known to be substantially excreted by the kidney, and the risk of toxic reactions to this drug may be greater in patients with impaired renal function. Because elderly patients are more likely to have decreased renal function, care should be taken in dose selection, and it may be useful to monitor renal function (see DOSAGE AND ADMINISTRATION).

ADVERSE REACTIONS

Cefuroxime for Injection is generally well tolerated. The most common adverse effects have been local reactions following IV administration. Other adverse reactions have been encountered only rarely.

Local Reactions

Thrombophlebitis has occurred with IV administration in 1 in 60 patients.

Gastrointestinal

Gastrointestinal symptoms occurred in 1 in 150 patients and included diarrhea (1 in 220 patients) and nausea (1 in 440 patients). The onset of pseudomembranous colitis may occur during or after antibacterial treatment (see WARNINGS).

Hypersensitivity Reactions

Hypersensitivity reactions have been reported in fewer than 1% of the patients treated with Cefuroxime for Injection and include rash (1 in 125). Pruritus, urticaria, and positive Coombs' test each occurred in fewer than 1 in 250 patients, and, as with other cephalosporins, rare cases of anaphylaxis, drug fever, erythema multiforme, interstitial nephritis, toxic epidermal necrolysis, and Stevens-Johnson syndrome have occurred.

Blood

A decrease in hemoglobin and hematocrit has been observed in 1 in 10 patients and transient eosinophilia in 1 in 14 patients. Less common reactions seen were transient neutropenia (fewer than 1 in 100 patients) and leukopenia (1 in 750 patients). A similar pattern and incidence were seen with other cephalosporins used in controlled studies. As with other cephalosporins, there have been rare reports of thrombocytopenia.

Hepatic

Transient rise in SGOT and SGPT (1 in 25 patients), alkaline phosphatase (1 in 50 patients), LDH (1 in 75 patients), and bilirubin (1 in 500 patients) levels has been noted.

Kidney

Elevations in serum creatinine and/or blood urea nitrogen and a decreased creatinine clearance have been observed, but their relationship to cefuroxime is unknown.

Postmarketing Experience with Cefuroxime for Injection

In addition to the adverse events reported during clinical trials, the following events have been observed during clinical practice in patients treated with Cefuroxime for Injection and were reported spontaneously. Data are generally insufficient to allow an estimate of incidence or to establish causation.

Immune System Disorders: Cutaneous vasculitis, angioedema, acute myocardial ischemia with or without myocardial infarction may occur as part of an allergic reaction.

Nervous System Disorders: Seizure

Cephalosporin-class Adverse Reactions

In addition to the adverse reactions listed above that have been observed in patients treated with cefuroxime, the following adverse reactions and altered laboratory tests have been reported for cephalosporin-class antibiotics:

Adverse Reactions

Vomiting, abdominal pain, colitis, vaginitis including vaginal candidiasis, toxic nephropathy, hepatic dysfunction including cholestasis, aplastic anemia, hemolytic anemia, hemorrhage.

Several cephalosporins, including Cefuroxime for Injection, have been implicated in triggering seizures, particularly in patients with renal impairment when the dosage was not reduced (see DOSAGE AND ADMINISTRATION). If seizures associated with drug therapy should occur, the drug should be discontinued. Anticonvulsant therapy can be given if clinically indicated.

Altered Laboratory Tests

Prolonged prothrombin time, pancytopenia, agranulocytosis.

To report SUSPECTED ADVERSE REACTIONS, contact Sagent Pharmaceuticals, Inc. at 1-866-625-1618 or FDA at 1-800-FDA-1088 or www.fda.gov/medwatch.

OVERDOSAGE

Overdosage of cephalosporins can cause cerebral irritation leading to convulsions. Serum levels of cefuroxime can be reduced by hemodialysis and peritoneal dialysis.

DOSAGE AND ADMINISTRATION

Dosage

Adults

The usual adult dosage range for Cefuroxime for Injection is 750 mg to 1.5 grams every 8 hours, usually for 5 to 10 days. In uncomplicated urinary tract infections, skin and skin-structure infections, disseminated gonococcal infections, and uncomplicated pneumonia, a 750-mg dose every 8 hours is recommended. In severe or complicated infections, a 1.5-gram dose every 8 hours is recommended.

In bone and joint infections, a 1.5-gram dose every 8 hours is recommended. In clinical trials, surgical intervention was performed when indicated as an adjunct to therapy with Cefuroxime for Injection. A course of oral antibiotics was administered when appropriate following the completion of parenteral administration of Cefuroxime for Injection.

In life-threatening infections or infections due to less susceptible organisms, 1.5 grams every 6 hours may be required. In bacterial meningitis, the dosage should not exceed 3 grams every 8 hours. The recommended dosage for uncomplicated gonococcal infection is 1.5 grams given intramuscularly as a single dose at 2 different sites together with 1 gram of oral probenecid. For preventive use for clean-contaminated or potentially contaminated surgical procedures, a 1.5-gram dose administered intravenously just before surgery (approximately one-half to 1 hour before the initial incision) is recommended. Thereafter, give 750 mg intravenously or intramuscularly every 8 hours when the procedure is prolonged.

For preventive use during open heart surgery, a 1.5-gram dose administered intravenously at the induction of anesthesia and every 12 hours thereafter for a total of 6 grams is recommended.

Impaired Renal Function

A reduced dosage must be employed when renal function is impaired. Dosage should be determined by the degree of renal impairment and the susceptibility of the causative organism (see Table 2).

Table 2. Dosage of Cefuroxime for Injection in Adults with Reduced Renal Function
Creatinine Clearance (mL/min) | Dose | Frequency
> 20 | 750 mg to 1.5 grams | q8h
10 to 20 | 750 mg | q12h
< 10 | 750 mg | q24ha
a Since Cefuroxime for Injection is dialyzable, patients on hemodialysis should be given a further dose at the end of the dialysis.

When only serum creatinine is available, the following formula^1 (based on sex, weight, and age of the patient) may be used to convert this value into creatinine clearance. The serum creatinine should represent a steady state of renal function.

NOTE: As with antibiotic therapy in general, administration of Cefuroxime for Injection should be continued for a minimum of 48 to 72 hours after the patient becomes asymptomatic or after evidence of bacterial eradication has been obtained; a minimum of 10 days of treatment is recommended in infections caused by Streptococcus pyogenes in order to guard against the risk of rheumatic fever or glomerulonephritis; frequent bacteriologic and clinical appraisal is necessary during therapy of chronic urinary tract infection and may be required for several months after therapy has been completed; persistent infections may require treatment for several weeks; and doses smaller than those indicated above should not be used. In staphylococcal and other infections involving a collection of pus, surgical drainage should be carried out where indicated.

Pediatric Patients Above 3 Months of Age

Administration of 50 to 100 mg/kg/day in equally divided doses every 6 to 8 hours has been successful for most infections susceptible to cefuroxime. The higher dosage of 100 mg/kg/day (not to exceed the maximum adult dosage) should be used for the more severe or serious infections.

In bone and joint infections, 150 mg/kg/day (not to exceed the maximum adult dosage) is recommended in equally divided doses every 8 hours. In clinical trials, a course of oral antibiotics was administered to pediatric patients following the completion of parenteral administration of Cefuroxime for Injection.

In cases of bacterial meningitis, a larger dosage of Cefuroxime for Injection is recommended, 200 to 240 mg/kg/day intravenously in divided doses every 6 to 8 hours.

In pediatric patients with renal insufficiency, the frequency of dosing should be modified consistent with the recommendations for adults.

Preparation of Solution and Suspension

The directions for preparing Cefuroxime for Injection for both IV and IM use are summarized in Table 3.

For Intramuscular Use

Each 750-mg vial of Cefuroxime for Injection should be constituted with 3 mL of Sterile Water for Injection. Shake gently to disperse and withdraw completely the resulting suspension for injection.

For Intravenous Use

Each 750-mg vial should be constituted with 8.3 mL of Sterile Water for Injection. Withdraw completely the resulting solution for injection.

Each 1.5-gram vial should be constituted with 16 mL of Sterile Water for Injection, and the solution should be completely withdrawn for injection.

Table 3. Preparation of Solution and Suspension
Strength | Amount of Diluent to be Added (mL) | Volume to be Withdrawn | Approximate Cefuroxime Concentration (mg/mL)
750-mg Vial | 3 (IM) | Totala | 225
750-mg Vial | 8.3 (IV) | Total | 90
1.5-gram Vial | 16 (IV) | Total | 90
a Note: Cefuroxime for Injection is a suspension at IM concentrations.

Administration

After constitution, Cefuroxime for Injection may be given intravenously or by deep IM injection into a large muscle mass (such as the gluteus or lateral part of the thigh). Before injecting intramuscularly, aspiration is necessary to avoid inadvertent injection into a blood vessel.

Intravenous Administration

The IV route may be preferable for patients with bacterial septicemia or other severe or life-threatening infections or for patients who may be poor risks because of lowered resistance, particularly if shock is present or impending.

For direct intermittent IV administration, slowly inject the solution into a vein over a period of 3 to 5 minutes or give it through the tubing system by which the patient is also receiving other IV solutions.

For intermittent IV infusion with a Y-type administration set, dosing can be accomplished through the tubing system by which the patient may be receiving other IV solutions. However, during infusion of the solution containing Cefuroxime for Injection, it is advisable to temporarily discontinue administration of any other solutions at the same site.

For continuous IV infusion, a solution of Cefuroxime for Injection may be added to an IV infusion pack containing one of the following fluids: 0.9% Sodium Chloride Injection; 5% Dextrose Injection; 10% Dextrose Injection; 5% Dextrose and 0.9% Sodium Chloride Injection; 5% Dextrose and 0.45% Sodium Chloride Injection; or 1/6 M Sodium Lactate Injection.

Solutions of Cefuroxime for Injection, like those of most beta-lactam antibiotics, should not be added to solutions of aminoglycoside antibiotics because of potential interaction.

However, if concurrent therapy with Cefuroxime for Injection and an aminoglycoside is indicated, each of these antibiotics can be administered separately to the same patient.

COMPATIBILITY AND STABILITY

Intramuscular

When constituted as directed with Sterile Water for Injection, suspensions of cefuroxime for IM injection maintain satisfactory potency for 24 hours at room temperature and for 48 hours under refrigeration (5°C).

After the periods mentioned above any unused suspensions should be discarded.

Intravenous

When the 750-mg and 1.5-g vials are constituted as directed with Sterile Water for Injection, the solutions of Cefuroxime for Injection for IV administration maintain satisfactory potency for 24 hours at room temperature and for 48 hours (750-mg and 1.5-g vials) under refrigeration (5°C). More dilute solutions, such as 750 mg or 1.5 g plus 100 mL of Sterile Water for Injection, 5% Dextrose Injection, or 0.9% Sodium Chloride Injection, also maintain satisfactory potency for 24 hours at room temperature and for 7 days under refrigeration.

These solutions may be further diluted to concentrations of between 1 and 30 mg/mL in the following solutions and will lose not more than 10% activity for 24 hours at room temperature or for at least 7 days under refrigeration: 0.9% Sodium Chloride Injection; 1/6 M Sodium Lactate Injection; Ringer's Injection, USP; Lactated Ringer's Injection, USP; 5% Dextrose and 0.9% Sodium Chloride Injection; 5% Dextrose Injection; 5% Dextrose and 0.45% Sodium Chloride Injection; 5% Dextrose and 0.225% Sodium Chloride Injection; 10% Dextrose Injection; and 10% Invert Sugar in Water for Injection.

Unused solutions should be discarded after the time periods mentioned above.

Cefuroxime for Injection has also been found compatible for 24 hours at room temperature when admixed in IV infusion with heparin (10 and 50 U/mL) in 0.9% Sodium Chloride Injection and Potassium Chloride (10 and 40 mEq/L) in 0.9% Sodium Chloride Injection. Sodium Bicarbonate Injection, USP is not recommended for the dilution of Cefuroxime for Injection.

Frozen Stability

Constitute the 750-mg or 1.5-g vial as directed for IV administration in Table 3. Immediately withdraw the total contents of the 750-mg or 1.5-g vial and add to a compatible container containing 50 or 100 mL of 0.9% Sodium Chloride Injection or 5% Dextrose Injection and freeze. Frozen solutions are stable for 6 months when stored at -20°C. Frozen solutions should be thawed at room temperature and not refrozen. Do not force thaw by immersion in water baths or by microwave irradiation. Thawed solutions may be stored for up to 24 hours at room temperature or for 7 days in a refrigerator.

Note: Parenteral drug products should be inspected visually for particulate matter and discoloration before administration whenever solution and container permit.

As with other cephalosporins, Cefuroxime for Injection powder as well as solutions and suspensions tend to darken, depending on storage conditions, without adversely affecting product potency.

HOW SUPPLIED

Cefuroxime for Injection, USP is supplied as follows:

NDC | Cefuroxime for Injection, USP | Package Factor
25021-118-10 | 750 mg equivalent of cefuroxime | 25 vials per carton
 | in a Single-Dose Vial
25021-119-20 | 1.5 grams equivalent of cefuroxime | 25 vials per carton
 | in a Single-Dose Vial

Cefuroxime for Injection, USP is a dry, white to off-white powder.

Storage Conditions

Store at 20° to 25°C (68° to 77°F). [See USP Controlled Room Temperature.]

Protect from light.

Sterile, Nonpyrogenic, Preservative-free.

The container closure is not made with natural rubber latex.

REFERENCES

1. Cockcroft DW, Gault MH. Prediction of creatinine clearance from serum creatinine. Nephron. 1976; 16:31-41.

Brands listed are the trademarks of their respective owners.

SAGENT®
Mfd. for SAGENT Pharmaceuticals
Schaumburg, IL 60195 (USA)
Made in Italy
©2021 Sagent Pharmaceuticals, Inc.

Revised: June 2021

SAGENT Pharmaceuticals®

PACKAGE LABEL – PRINCIPAL DISPLAY PANEL – Vial Label

NDC 25021-119-20

Rx only

CEFUROXIME FOR INJECTION, USP

1.5 grams per vial

Equivalent to 1.5 grams of cefuroxime activity

Single-Dose Vial

For Intravenous Use

PACKAGE LABEL – PRINCIPAL DISPLAY PANEL – Vial Label

NDC 25021-118-10

Rx only

CEFUROXIME FOR INJECTION, USP

750 mg per vial

Equivalent to 750 mg of cefuroxime activity

Single-Dose Vial

For Intravenous or Intramuscular Use